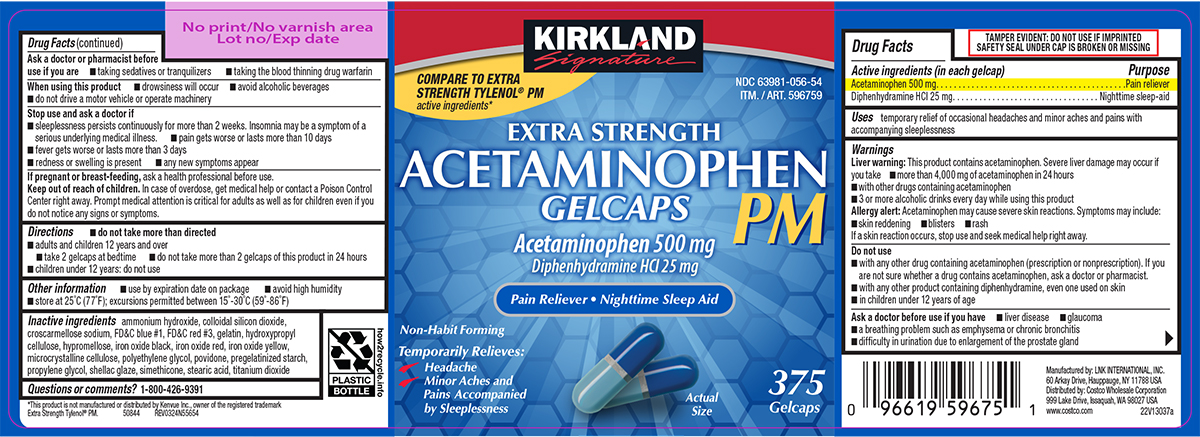 DRUG LABEL: Acetaminophen PM
NDC: 63981-056 | Form: TABLET, COATED
Manufacturer: COSTCO WHOLESALE CORPORATION
Category: otc | Type: HUMAN OTC DRUG LABEL
Date: 20250912

ACTIVE INGREDIENTS: ACETAMINOPHEN 500 mg/1 1; DIPHENHYDRAMINE HYDROCHLORIDE 25 mg/1 1
INACTIVE INGREDIENTS: AMMONIA; SILICON DIOXIDE; CROSCARMELLOSE SODIUM; FD&C BLUE NO. 1; FD&C RED NO. 3; GELATIN, UNSPECIFIED; HYDROXYPROPYL CELLULOSE, UNSPECIFIED; HYPROMELLOSE, UNSPECIFIED; FERROSOFERRIC OXIDE; FERRIC OXIDE RED; FERRIC OXIDE YELLOW; MICROCRYSTALLINE CELLULOSE; POLYETHYLENE GLYCOL, UNSPECIFIED; POVIDONE, UNSPECIFIED; STARCH, CORN; PROPYLENE GLYCOL; SHELLAC; STEARIC ACID; TITANIUM DIOXIDE

Kirkland 44-556-Acetaminophen PM

Active ingredients (in each gelcap)

Acetaminophen 500 mg
Diphenhydramine HCl 25 mg

Purpose

Pain reliever
Nighttime sleep-aid

Uses

temporary relief of occasional headaches and minor aches and pains with accompanying sleeplessness

Warnings

Liver warning: This product contains acetaminophen. Severe liver damage may occur if you take

- more than 4,000 mg of acetaminophen in 24 hours
- with other drugs containing acetaminophen
- 3 or more alcoholic drinks every day while using this product

Allergy alert: Acetaminophen may cause severe skin reactions. Symptoms may include:

- skin reddening
- blisters
- rash

If a skin reaction occurs, stop use and seek medical help right away.

Do not use

- with any other drug containing acetaminophen (prescription or nonprescription). If you are not sure whether a drug contains acetaminophen, ask a doctor or pharmacist.
- in children under 12 years of age
- with any other product containing diphenhydramine, even one used on skin

Ask a doctor before use if you have

- liver disease
- glaucoma
- a breathing problem such as emphysema or chronic bronchitis
- difficulty in urination due to enlargement of the prostate gland

Ask a doctor or pharmacist before use if you are

- taking sedatives or tranquilizers
- taking the blood thinning drug warfarin

When using this product

- drowsiness will occur
- avoid alcoholic beverages
- do not drive a motor vehicle or operate machinery

Stop use and ask a doctor if

- any new symptoms appear
- redness or swelling is present
- sleeplessness persists continuously for more than 2 weeks. Insomnia may be a symptom of a serious underlying medical illness.
- pain gets worse or lasts more than 10 days
- fever gets worse or lasts more than 3 days

If pregnant or breast-feeding,

ask a health professional before use.

Keep out of reach of children.

In case of overdose, get medical help or contact a Poison Control Center right away. Prompt medical attention is critical for adults as well as for children even if you do not notice any signs or symptoms.

Directions

- do not take more than directed
- adults and children 12 years and over
  - take 2 gelcaps at bedtime
  - do not take more than 2 gelcaps of this product in 24 hours
- children under 12 years: do not use

Other information

- use by expiration date on package
- avoid high humidity
- store at 25°C (77°F); excursions permitted between 15°-30°C (59°-86°F)

Inactive ingredients

ammonium hydroxide, colloidal silicon dioxide, croscarmellose sodium, FD&C blue #1, FD&C red #3, gelatin, hydroxypropyl cellulose, hypromellose, iron oxide black, iron oxide red, iron oxide yellow, microcrystalline cellulose, polyethylene glycol, povidone, pregelatinized starch, propylene glycol, shellac glaze, simethicone, stearic acid, titanium dioxide

Questions or comments?

1-800-426-9391

Principal display panel

KIRKLAND
Signature

COMPARE TO EXTRA
STRENGTH TYLENOL® PM
active ingredients*

NDC 63981-056-54
ITM. / ART. 596759

EXTRA STRENGTH
ACETAMINOPHEN PM
GELCAPS

Acetaminophen 500 mg
Diphenhydramine HCl 25 mg

Pain Reliever • Nighttime Sleep Aid

Non-Habit Forming

Temporarily Relieves:
• Headache
• Minor Aches and
Pains Accompanied
by Sleeplessness

Actual
Size

375
Gelcaps

TAMPER EVIDENT: DO NOT USE IF IMPRINTED
SAFETY SEAL UNDER CAP IS BROKEN OR MISSING

*This product is not manufactured or distributed by Kenvue Inc., owner of the registered trademark
Extra Strength Tylenol® PM. 50844 REV0324N55654

Manufactured by: LNK INTERNATIONAL, INC.
60 Arkay Drive, Hauppauge, NY 11788 USA
Distributed by: Costco Wholesale Corporation
999 Lake Drive, Issaquah, WA 98027 USA
www.costco.com 22V13037a

Kirkland 44-556